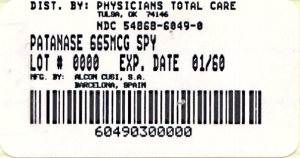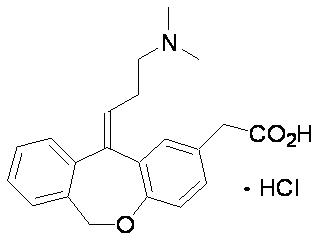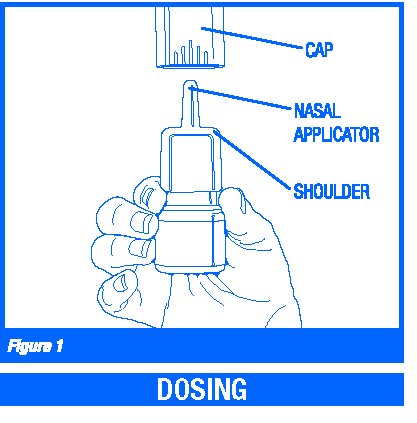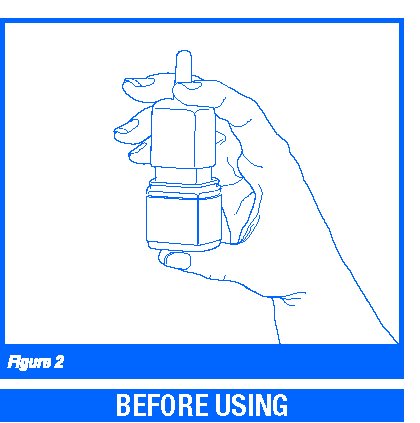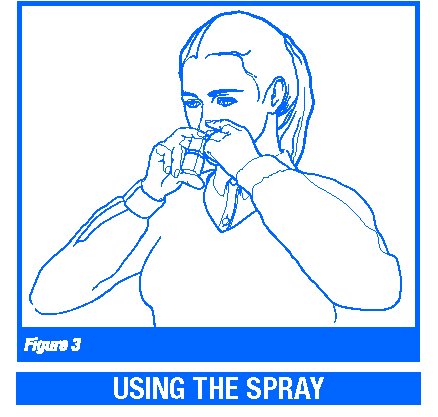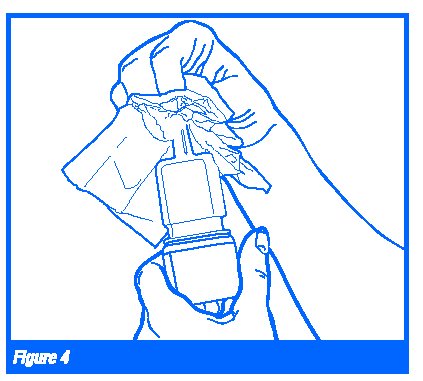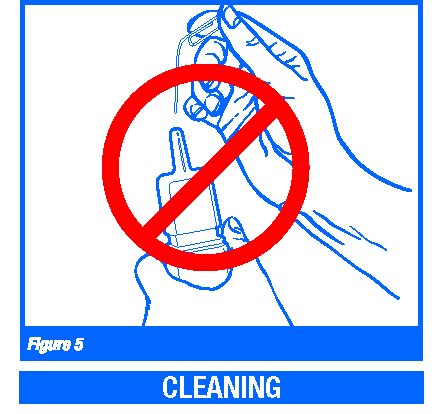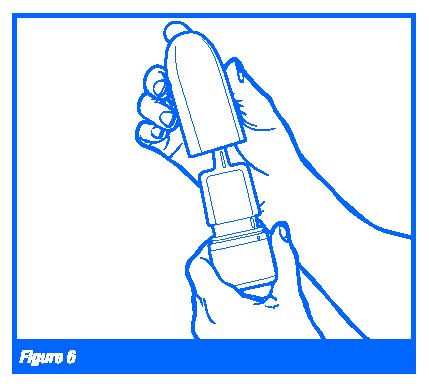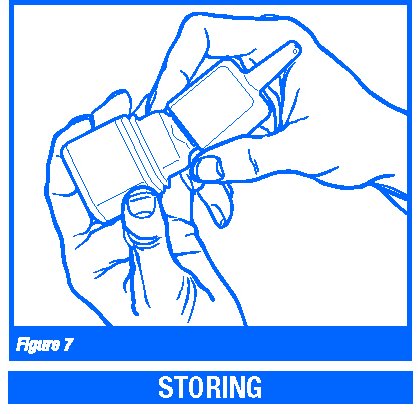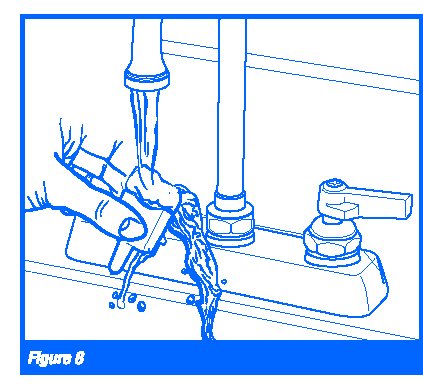 DRUG LABEL: PATANASE
NDC: 54868-6049 | Form: SPRAY, METERED
Manufacturer: Physicians Total Care, Inc.
Category: prescription | Type: HUMAN PRESCRIPTION DRUG LABEL
Date: 20120116

ACTIVE INGREDIENTS: OLOPATADINE HYDROCHLORIDE 665 ug/1 1
INACTIVE INGREDIENTS: BENZALKONIUM CHLORIDE; SODIUM PHOSPHATE, DIBASIC; EDETATE DISODIUM; SODIUM CHLORIDE; HYDROCHLORIC ACID; SODIUM HYDROXIDE; WATER

HIGHLIGHTS OF PRESCRIBING INFORMATION

These highlights do not include all the information needed to use PATANASE® Nasal Spray safely and effectively. See full prescribing information for PATANASE Nasal Spray.
PATANASE (olopatadine hydrochloride) Nasal Spray
Initial U.S. Approval: 1996

1 INDICATIONS AND USAGE

PATANASE Nasal Spray is an H1 receptor antagonist indicated for the relief of the symptoms of seasonal allergic rhinitis in adults and children 6 years of age and older. (1)

2 DOSAGE AND ADMINISTRATION

For intranasal use only.

Recommended dosages:

• Adults and adolescents ≥12 years: Two sprays per nostril twice daily. (2.1)

• Children 6 to 11 years: One spray per nostril twice daily. (2.2)

Priming Information: Prime PATANASE Nasal Spray before initial use and when PATANASE Nasal Spray has not been used for more than 7 days. (2.3)

3 DOSAGE FORMS AND STRENGTHS

Nasal spray 0.6%: 665 mcg of olopatadine hydrochloride in each 100- microliter spray. (3) Supplied as a 30.5 g bottle containing 240 sprays.

4 CONTRAINDICATIONS

None.

5 WARNINGS AND PRECAUTIONS

• Epistaxis, nasal ulceration, and nasal septal perforation. Monitor patients periodically for signs of adverse effects on the nasal mucosa. Discontinue if ulcerations or perforations occur. Avoid use in patients with nasal disease other than allergic rhinitis (5.1).

• Avoid engaging in hazardous occupations requiring complete mental alertness and coordination such as driving or operating machinery when taking PATANASE Nasal Spray (5.2).

• Avoid concurrent use of alcohol or other central nervous system depressants with PATANASE Nasal Spray (5.2).

6 ADVERSE REACTIONS

The most common (>1%) adverse reactions included bitter taste, headache, epistaxis, pharyngolaryngeal pain, post-nasal drip, cough, and urinary tract infection in patients 12 years of age and older and epistaxis, headache, upper respiratory tract infection, bitter taste, pyrexia, and rash in patients 6 to 11 years of age (6.1).

To report SUSPECTED ADVERSE REACTIONS, contact Alcon Laboratories, Inc. at 1-800-757-9195 or FDA at 1-800-FDA-1088 or www.fda.gov/medwatch.

FULL PRESCRIBING INFORMATION

1 INDICATIONS AND USAGE

1.1 Seasonal Allergic Rhinitis

PATANASE Nasal Spray is an H1 receptor antagonist indicated for the relief of the symptoms of seasonal allergic rhinitis in adults and children 6 years of age and older.

2 DOSAGE AND ADMINISTRATION

Administer PATANASE Nasal Spray by the intranasal route only.

2.1 Adults and Adolescents 12 years of age and older

The recommended dosage is two sprays per nostril twice daily.

2.2 Children 6 to 11 years of age

The recommended dosage is one spray per nostril twice daily.

2.3 Administration Information

Priming: Before initial use, prime PATANASE Nasal Spray by releasing 5 sprays or until a fine mist appears. When PATANASE Nasal Spray has not been used for more than 7 days, re-prime by releasing 2 sprays. Avoid spraying PATANASE Nasal Spray into the eyes.

3 DOSAGE FORMS AND STRENGTHS

PATANASE Nasal Spray is a nasal spray solution supplied in a white plastic bottle with a metered-dose manual spray pump, a white nasal applicator, and a blue overcap. Each spray (100 microliters) delivers 665 mcg of olopatadine hydrochloride.

4 CONTRAINDICATIONS

None.

5 WARNINGS AND PRECAUTIONS

5.1 Local Nasal Effects

Epistaxis and Nasal Ulceration: In placebo (vehicle nasal spray)-controlled clinical trials of 2 weeks to 12 months duration, epistaxis and nasal ulcerations were reported [see Adverse Reactions (6)].

Nasal Septal Perforation:

Two placebo (vehicle nasal spray)-controlled long term (12 months) safety trials were conducted. In the first safety trial, patients were treated with an investigational formulation of PATANASE Nasal Spray containing povidone (not the commercially marketed formulation) or a vehicle nasal spray containing povidone. Nasal septal perforations were reported in one patient treated with the investigational formulation of PATANASE Nasal Spray and 2 patients treated with the vehicle nasal spray. In the second safety trial with PATANASE Nasal Spray, which does not contain povidone, there were no reports of nasal septal perforation [see Adverse Reactions (6)].

Before starting PATANASE Nasal Spray, conduct a nasal examination to ensure that patients are free of nasal disease other than allergic rhinitis. Perform nasal examinations periodically for signs of adverse effects on the nasal mucosa and consider stopping PATANASE Nasal Spray if patients develop nasal ulcerations.

5.2 Activities Requiring Mental Alertness

In clinical trials, the occurrence of somnolence has been reported in some patients taking PATANASE Nasal Spray [see Adverse Reactions (6)]. Patients should be cautioned against engaging in hazardous occupations requiring complete mental alertness and motor coordination such as driving or operating machinery after administration of PATANASE Nasal Spray. Concurrent use of PATANASE Nasal Spray with alcohol or other central nervous system depressants should be avoided because additional reductions in alertness and additional impairment of central nervous system performance may occur.

6 ADVERSE REACTIONS

Use of PATANASE Nasal Spray has been associated with epistaxis, nasal ulcerations, and somnolence [see Warnings and Precautions (5.1 and 5.2)].

6.1 Clinical Trials Experience

The safety data described below reflect exposure to PATANASE Nasal Spray in 2,427 patients with seasonal or perennial allergic rhinitis in 9 controlled clinical trials of 2 weeks to 12 months duration.

The safety data from adults and adolescents are based upon 5 placebo (vehicle nasal spray)-controlled clinical trials in which 1,491 patients with seasonal or perennial allergic rhinitis (513 males and 978 females) 12 years of age and older were treated with PATANASE Nasal Spray two sprays per nostril twice daily. There were 1,180 patients (PATANASE Nasal Spray, 587; vehicle nasal spray, 593) that participated in 3 efficacy and safety trials of 2 weeks duration. There were 1,814 patients (PATANASE Nasal Spray, 904; vehicle nasal spray, 910) that participated in 2 long-term clinical trials of 1 year duration. The racial distribution of adult and adolescent patients receiving PATANASE Nasal Spray was 76% white, 8% black, 12% Hispanic and 3% other. The incidence of discontinuation due to adverse reactions in these controlled clinical trials was comparable for PATANASE Nasal Spray and vehicle nasal spray. Overall, 3.9% of the 1,491 adult and adolescent patients across all 5 studies treated with PATANASE Nasal Spray and 3.2% of the 1,503 patients treated with vehicle nasal spray discontinued due to adverse reactions.

The safety data from pediatric patients 6-11 years of age are based upon 3 clinical trials in which 870 children with seasonal allergic rhinitis (376 females and 494 males) were treated with PATANASE Nasal Spray 1 or 2 sprays per nostril twice daily for 2 weeks. The racial distribution of pediatric patients receiving PATANASE Nasal Spray was 68.6% white, 16.6% black, and 14.8% other. The incidence of discontinuation due to adverse reactions in these controlled clinical trials was comparable for PATANASE Nasal Spray and vehicle nasal spray.

Overall, 1.4% of the 870 pediatric patients across all 3 studies treated with PATANASE Nasal Spray and 1.3% of the 872 pediatric patients treated with vehicle nasal spray discontinued due to adverse reactions. Safety information for pediatric patients 2 to 5 years of age is obtained from one vehicle-controlled study of 2 weeks duration [See Pediatric Use (8.4)].

Because clinical trials are conducted under widely varying conditions, adverse reaction rates observed in the clinical trials of a drug cannot be directly compared to rates in the clinical trials of another drug and may not reflect the rates observed in practice.

Adults and Adolescents 12 Years of Age and Older in Short-Term (2-week) Trials: There were 1,180 patients 12 years of age and older (PATANASE Nasal Spray, 587; vehicle nasal spray, 593) that participated in 3 efficacy and safety trials of 2 weeks duration. Table 1 presents the most common adverse reactions (0.9% or greater in patients treated with PATANASE Nasal Spray) that occurred more frequently in patients treated with PATANASE Nasal Spray compared with vehicle nasal spray in the 3 clinical trials of 2 weeks duration.

Table 1: Adverse Reactions Occurring at an Incidence of 0.9% or Greater in Controlled Clinical Trials of 2 Weeks Duration with PATANASE Nasal Spray in Adolescent and Adult Patients 12 Years of Age and Older with Seasonal Allergic Rhinitis

 | Adult and Adolescent Patients 12 Years and Older
Adverse Reaction | PATANASE Nasal Spray N = 587 | Vehicle Nasal Spray N = 593
Bitter taste | 75 (12.8%) | 5 (0.8%)
Headache | 26 (4.4%) | 24 (4.0%)
Epistaxis | 19 (3.2%) | 10 (1.7%)
Pharyngolaryngeal Pain | 13 (2.2%) | 8 (1.3%)
Post-nasal drip | 9 (1.5%) | 5 (0.8%)
Cough | 8 (1.4%) | 3 (0.5%)
Urinary tract infection | 7 (1.2%) | 3 (0.5%)
CPK elevation | 5 (0.9%) | 2 (0.3%)
Dry mouth | 5 (0.9%) | 1 (0.2%)
Fatigue | 5 (0.9%) | 4 (0.7%)
Influenza | 5 (0.9%) | 1 (0.2%)
Nasopharyngitis | 5 (0.9%) | 4 (0.7%)
Somnolence | 5 (0.9%) | 2 (0.3%)
Throat irritation | 5 (0.9%) | 0 (0.0%)

There were no differences in the incidence of adverse reactions based on gender or race.

Clinical trials did not include sufficient numbers of patients 65 years of age and older to determine whether they respond differently from younger subjects.

Pediatric Patients 6 to 11 Years of Age: There were 1,742 pediatric patients 6 to 11 years of age (Olopatadine nasal spray, 870; vehicle nasal spray, 872) with seasonal allergic rhinitis that participated in 3 clinical trials of 2 weeks duration. Two of the studies used the investigational formulation of olopatadine nasal spray, and one of the studies used PATANASE Nasal Spray. One study evaluated the safety of PATANASE Nasal Spray at doses of 1 and 2 sprays per nostril twice daily in 1188 patients, in which 298 were exposed to PATANASE 1 spray, 296 were exposed to PATANASE 2 sprays, 297 were exposed to vehicle 1 spray, and 297 were exposed to vehicle 2 sprays twice daily for 2 weeks. Table 2 presents the most common adverse reactions (greater than 1.0% in pediatric patients 6-11 years of age treated with PATANASE Nasal Spray 1 spray/nostril) that occurred more frequently with PATANASE Nasal Spray compared with vehicle nasal spray.

Table 2. Adverse Reactions Occurring at an Incidence of Greater than 1.0% in a Controlled Clinical Trial of 2 Weeks Duration with PATANASE Nasal Spray in Pediatric Patients 6-11 Years of Age With Seasonal Allergic Rhinitis

 | Pediatric Patients 6 to 11 Years of Age
Adverse Reaction | PATANASE Nasal Spray 1 spray per nostril N = 298 | Vehicle Nasal Spray 1 spray per nostril N = 297
Epistaxis Headache Upper respiratory tract infection Bitter taste | 17 (5.7%) 13 (4.4%) 8 (2.6%) 3 (1.0%) | 11 (3.7%) 11 (3.7%) 0 0
Pyrexia | 4 (1.3%) | 3 (1.0%)
Rash | 4 (1.3%) | 0

There were no differences in the incidence of adverse reactions based on gender, race, or ethnicity.

The safety of PATANASE Nasal Spray at a dose of 1 spray per nostril twice daily was evaluated in one 2- week vehicle-controlled study in 132 patients (PATANASE Nasal Spray, 66; vehicle nasal spray. 66) 2 to 5 years of age with allergic rhinitis [see Pediatric Use (8.4)].

Long-Term (12-month) Safety Trials:

In a 12-month, placebo (vehicle nasal spray)-controlled, safety trial, 890 patients 12 years of age and older with perennial allergic rhinitis were randomized to treatment with PATANASE Nasal Spray 2 sprays per nostril twice daily (445 patients) or vehicle nasal spray (445 patients). In the PATANASE and vehicle nasal spray groups, 72% and 74% of patients, respectively, completed the trial. Overall, 7% and 5%, respectively, discontinued study participation due to an adverse event. The most frequently reported adverse reaction was epistaxis, which occurred in 25% of patients treated with PATANASE Nasal Spray and 28% in patients treated with vehicle nasal spray. Epistaxis resulted in discontinuation of 0.9% of patients treated with PATANASE Nasal Spray and 0.2% of patients treated with vehicle nasal spray. Nasal ulcerations occurred in 10% of patients treated with PATANASE Nasal Spray and 9% of patients treated with vehicle nasal spray. Nasal ulcerations resulted in discontinuation of 0.4% of patients treated with PATANASE Nasal Spray and 0.2% patients treated with vehicle nasal spray. There were no patients with nasal septal perforation in either treatment group. Somnolence was reported in 1 patient treated with PATANASE Nasal Spray and 1 patient treated with vehicle nasal spray. Weight increase was reported in 6 patients treated with PATANASE Nasal Spray and 1 patient treated with vehicle nasal spray. Depression or worsening of depression occurred in 9 patients treated with PATANASE Nasal Spray and in 5 patients treated with vehicle nasal spray. Three patients, two of whom had pre-existing histories of depression, who received PATANASE Nasal Spray were hospitalized for depression compared to none who received vehicle nasal spray.

In a second 12-month, placebo (vehicle nasal spray)-controlled, safety trial, 459 patients 12 years of age and older with perennial allergic rhinitis were treated with 2 sprays per nostril of an investigational formulation of PATANASE Nasal Spray containing povidone (not the commercially marketed formulation) and 465 patients were treated with 2 sprays of a vehicle nasal spray containing povidone. Nasal septal perforations were reported in one patient treated with the investigational formulation of PATANASE Nasal Spray and 2 patients treated with the vehicle nasal spray. Epistaxis was reported in 19% of patients treated with the investigational formulation of PATANASE Nasal Spray and 12% of patients treated with vehicle nasal spray. Somnolence was reported in 3 patients treated with the investigational formulation of PATANASE Nasal Spray compared to 1 patient treated with vehicle nasal spray. Fatigue was reported in 5 patients treated with the investigational formulation of PATANASE Nasal Spray compared to 1 patient treated with vehicle nasal spray.

There were no long-term clinical trials in children below 12 years of age.

6.2 Post-Marketing Experience

The post-marketing adverse events reported post-approval are consistent with the adverse events reported during clinical trials. Because post-marketing adverse events are reported voluntarily from a population of uncertain size, it is not always possible to reliably estimate their frequency or establish a causal relationship to drug exposure.

7 DRUG INTERACTIONS

Formal drug-drug interaction studies were not conducted for PATANASE Nasal Spray. Drug interactions with inhibitors of liver enzymes are not anticipated because olopatadine is eliminated predominantly by renal excretion. Drug interactions involving P450 inhibition and plasma protein binding are also not expected. [See Clinical Pharmacology (12.3)].

8 USE IN SPECIFIC POPULATIONS

8.1 Pregnancy

Pregnancy Category C:

No adequate and well-controlled studies in pregnant women have been conducted. Animal reproductive studies in rats and rabbits revealed treatment-related effects on fetuses or pups. Because animal studies are not always predictive of human responses, PATANASE Nasal Spray should be used in pregnant women only if the potential benefit to the mother justifies the potential risk to the embryo or fetus.

A decrease in the number of live fetuses was observed in rabbits and rats at the oral olopatadine doses approximately 88 times and 100 times the maximum recommended human dose (MRHD) and above, respectively, for adults on a mg/m2 basis. In rats, viability and body weights of pups were reduced on day 4 post partum at the oral dose approximately 100 times the MRHD for adults on a mg/m2 basis, but no effect on viability was observed at the dose approximately 35 times the MRHD for adults on a mg/m2 basis.

8.3 Nursing Mothers

Olopatadine has been identified in the milk of nursing rats following oral administration. It is not known whether topical nasal administration could result in sufficient systemic absorption to produce detectable quantities in human breast milk. PATANASE Nasal Spray should be used by nursing mothers only if the potential benefit to the patient outweighs the potential risks to the infant.

8.4 Pediatric Use

The safety and effectiveness of PATANASE Nasal Spray has not been established for patients under 6 years of age. The safety of olopatadine nasal spray was evaluated in 3 vehicle-controlled 2-week studies in 870 patients 6 to 11 years of age [see Adverse Reactions (6.1)]. Doses studied included 1 and 2 sprays per nostril twice daily. One of these studies evaluated the safety of PATANASE Nasal Spray at doses of 1 and 2 sprays per nostril twice daily in 1188 patients, of which, 298 patients were exposed to PATANASE 1 spray and 297 patients were exposed to vehicle 1 spray. In this study, the incidence of epistaxis with PATANASE Nasal Spray treatment was 5.7%, compared to 3.2% seen in adult and adolescent studies. This study also evaluated the effectiveness of PATANASE Nasal Spray in patients 6 through 11 years of age with seasonal allergic rhinitis [see Clinical Studies (14.1)].

The safety of PATANASE Nasal Spray at a dose of 1 spray per nostril twice daily was evaluated in one 2-week vehicle-controlled study in 132 children ages 2 to 5 years of age with allergic rhinitis. In this trial, 66 patients (28 females and 38 males) were exposed to PATANASE Nasal Spray. The racial distribution of patients receiving PATANASE Nasal Spray was 66.7% white, 27.3% black, and 6.4% other. Two patients exposed to vehicle nasal spray discontinued due to an adverse reaction (1 patient with pneumonia and 1 patient with rhinitis) compared to no patients exposed to PATANASE Nasal Spray. The most common (greater than 1.0%) adverse events reported were diarrhea (9.1%), epistaxis (6.1%), rhinorrhea (4.5%), bitter taste (3.0%) and wheezing (3.0%). Diarrhea was reported less frequently (< 1%) in the 6 to 11 year old age group.

The incidence of epistaxis was higher in the pediatric population (5.7% in 6 -11 year old patients and 6.1% in 2-5 year old patients) compared to the adult and adolescent population (3.2%).

8.5 Geriatric Use

Clinical studies of PATANASE Nasal Spray did not include sufficient numbers of patients aged 65 years and older to determine whether they respond differently from younger patients. Other reported clinical experience has not identified differences in responses between the elderly and younger patients. In general, dose selection for an elderly patient should be cautious, reflecting the greater frequency of decreased hepatic, renal, or cardiac function and of concomitant disease or other drug therapy.

10 OVERDOSAGE

There have been no reported overdosages with PATANASE Nasal Spray.

Acute overdosage with this dosage form is unlikely due to the configuration of the primary container closure system. However, symptoms of antihistamine overdose may include drowsiness in adults and, initially, agitation and restlessness, followed by drowsiness in children. There is no known specific antidote to PATANASE Nasal Spray. Should overdose occur, symptomatic or supportive treatment is recommended, taking into account any concomitantly ingested medications.

No mortality was observed in rats at an intranasal dose of 3.6 mg/kg (approximately 6 times the MRHD for adults and adolescents ≥12 years of age and 7 times the MRHD for children 6-11 years of age on a mg/m2 basis), or in dogs at an oral dose of 5 g/kg (approximately 28,000 times the MRHD for adults and adolescents ≥12 years of age and 33,000 the MRHD for children 6-11 years of age on a mg/m2 basis). The oral median lethal dose (MLD) in mice and rats were 1,490 mg/kg and 3,870 mg/kg respectively (approximately 1,200 times and 6,500 times the MRHD for adults and adolescents ≥12 years of age and 1,500 times and 7,700 times the MRHD for children 6-11 years of age, on a mg/m2 basis, respectively).

For additional information about overdose treatment, call a poison control center (1-800-222-1222).

11 DESCRIPTION

PATANASE (olopatadine hydrochloride) Nasal Spray, 665 micrograms (mcg) is a metered-spray solution for intranasal administration. Olopatadine hydrochloride, the active component of PATANASE Nasal Spray, is a white, water-soluble crystalline powder. The chemical name for olopatadine hydrochloride is (Z)-11-[3-(dimethylamino)propylidene]-6,11-dihydrodibenz[b,e]oxepin-2-acetic acid hydrochloride. It has a molecular weight of 373.88, and its molecular formula is C21H23NO3 • HCl with the following chemical structure:

PATANASE Nasal Spray contains 0.6% w/v olopatadine (base) in a nonsterile aqueous solution with pH of approximately 3.7. After initial priming (5 sprays), each metered spray from the nasal applicator delivers 100 microliters of the aqueous solution containing 665 mcg of olopatadine hydrochloride, which is equivalent to 600 mcg of olopatadine (base) [see Dosage and Administration]. PATANASE Nasal Spray also contains benzalkonium chloride (0.01%), dibasic sodium phosphate, edetate disodium, sodium chloride, hydrochloric acid and/or sodium hydroxide (to adjust pH), and purified water.

12 CLINICAL PHARMACOLOGY

12.1 Mechanism of Action

Olopatadine is a histamine H1 -receptor antagonist. The antihistaminic activity of olopatadine has been documented in isolated tissues, animal models, and humans.

12.2 Pharmacodynamics

Cardiac effects: In a placebo-controlled cardiovascular safety study, 32 healthy volunteers received 20 mg oral solution of olopatadine twice daily for 14 days (8-fold greater daily dose than the recommended daily nasal dose). The mean QTcF (QT corrected by Fridericia's correction method for heart rate) change from baseline was -2.7 msec and -3.8 msec for olopatadine, and placebo, respectively. In this study, 8 subjects treated with olopatadine had a QTcF change from baseline of 30 - 60 msec, 1 subject had a QTcF change from baseline greater than 60 msec, and no subjects had QTcF values greater than 500 msec. Eight subjects treated with placebo had a QTcF change from baseline of 30 - 60 msec, no subjects had a QTcF change from baseline greater than 60 msec, and no subjects had QTcF values greater than 500 msec. In a 12-month study in 429 perennial allergic rhinitis patients treated with PATANASE Nasal Spray 2 sprays per nostril twice daily, no evidence of any effect of olopatadine hydrochloride on QT prolongation was observed.

12.3 Pharmacokinetics

The pharmacokinetic properties of olopatadine were studied after administration by the nasal, oral, intravenous, and topical ocular routes. Olopatadine exhibited linear pharmacokinetics across the routes studied over a large dose range.

Absorption:

Healthy Subjects: Olopatadine was absorbed with individual peak plasma concentrations observed between 30 minutes and 1 hour after twice daily intranasal administration of PATANASE Nasal Spray. The mean (± SD) steady-state peak plasma concentration (Cmax) of olopatadine was 16.0 ± 8.99 ng/mL. Systemic exposure as indexed by area under the curve (AUC0-12) averaged 66.0 ± 26.8 ng·h/mL. The average absolute bioavailability of intranasal olopatadine is 57%. The mean accumulation ratio following multiple intranasal administration of PATANASE Nasal Spray was about 1.3.

Seasonal Allergic Rhinitis (SAR) Patients: Systemic exposure of olopatadine in SAR patients after twice daily intranasal administration of PATANASE Nasal Spray was comparable to that observed in healthy subjects. Olopatadine was absorbed with peak plasma concentrations observed between 15 minutes and 2 hours. The mean steady-state Cmax was 23.3 ± 6.2 ng/mL and AUC0-12 averaged 78.0 ± 13.9 ng·h/mL.

Distribution: The protein binding of olopatadine was moderate at approximately 55% in human serum, and independent of drug concentration over the range of 0.1 to 1000 ng/mL. Olopatadine was bound predominately to human serum albumin.

Metabolism: Olopatadine is not extensively metabolized. Based on plasma metabolite profiles following oral administration of [^14C] olopatadine, at least six minor metabolites circulate in human plasma. Olopatadine accounts for 77% of peak plasma total radioactivity and all metabolites amounted to <6% combined. Two of these have been identified as the olopatadine N-oxide and N-desmethyl olopatadine. In in vitro studies with cDNA-expressed human cytochrome P450 isoenzymes (CYP) and flavin-containing monooxygenases (FMO), N-desmethyl olopatadine (Ml) formation was catalyzed mainly by CYP3A4, while olopatadine N-oxide (M3) was primarily catalyzed by FMO1 and FMO3. Olopatadine at concentrations up to 33,900 ng/mL did not inhibit the in vitro metabolism of specific substrates for CYP1A2, CYP2C9, CYP2C19, CYP2D6, CYP2E1 and CYP3A4. The potential for olopatadine and its metabolites to act as inducers of CYP enzymes has not been evaluated.

Elimination: The plasma elimination half-life of olopatadine is 8 to 12 hours. Olopatadine is mainly eliminated through urinary excretion. Approximately 70% of a [^14C] olopatadine hydrochloride oral dose was recovered in urine with 17% in the feces. Of the drug-related material recovered within the first 24 hours in the urine, 86% was unchanged olopatadine with the balance comprised of olopatadine N-oxide and N-desmethyl olopatadine.

Special Population:

Hepatic Impairment: No specific pharmacokinetic study examining the effect of hepatic impairment was conducted. Since metabolism of olopatadine is a minor route of elimination, no adjustment of the dosing regimen of PATANASE Nasal Spray is warranted in patients with hepatic impairment.

Renal Impairment: The mean Cmax values for olopatadine following single intranasal doses were not markedly different between healthy subjects (18.1 ng/mL) and patients with mild, moderate and severe renal impairment (range 15.5 to 21.6 ng/mL). Mean plasma AUC0-12 was two-fold higher in patients with severe impairment (creatinine clearance <30 mL/min/1.73 m2). In these patients, peak steady-state plasma concentrations of olopatadine are approximately 10-fold lower than those observed after higher 20 mg oral doses, twice daily, which were well-tolerated. These findings indicate that no adjustment of the dosing regimen of PATANASE Nasal Spray is warranted in patients with renal impairment.

Gender: The mean systemic exposure (Cmax and AUC0-12) in female SAR patients following multiple administration of olopatadine was 40% and 27% higher, respectively than those values observed in male SAR patients.

Race: The effects of race on olopatadine pharmacokinetics have not been adequately investigated.

Age: Pediatric Patients 6 to 11 Years of Age: The systemic pharmacokinetics of olopatadine, olopatadine N-oxide and Ndesmethyl olopatadine in patients 6 through 11 years of age were characterized using data from 42 pediatric patients administered PATANASE Nasal Spray, one spray per nostril twice daily for a minimum of 14 days. The mean Cmax (15.4 ± 7.3 ng/mL) of olopatadine was approximately 2-fold less than was comparable to that observed in adults (78.0 ± 13.9 ng·h/mL). The Cmax and AUC0-12 of olopatadine N-oxide were comparable to that observed in adults. The Cmax and AUC0-12 of N-desmethyl olopatadine are approximately 18% and 37% higher than that observed in adults, respectively.

Pediatric Patients 2 to 5 Years of Age: The systemic pharmacokinetics of olopatadine, olopatadine N-oxide, and N-desmethyl olopatadine were characterized using population pharmacokinetic methods applied to sparse data (approximately 5 samples per patient) obtained from 66 pediatric patients (2 to less than 6 years of age) administered one-half the recommended adult dose (1 spray per nostril) of PATANASE Nasal Spray twice daily for a minimum of 14 days. The mean Cmax and AUC0-12 of olopatadine were 13.4 ± 4.6 ng/mL and 75.0± 26.4 ng*hr/mL respectively. The mean Cmax and AUC0-12 of olopatdine N-oxide and N-desmethyl olopatadine were similar to that of patients 6 to 11 years of age.

Drug Interaction Studies

Drug interactions with inhibitors of liver enzymes are not anticipated because olopatadine is eliminated predominantly by renal excretion. Olopatadine did not inhibit the in vitro metabolism of specific substrates for CYP1A2, CYP2C9, CYP2C19, CYP2D6, CYP2E1 and CYP3A4. Based on these data, drug interactions involving P450 inhibition are not expected. Due to the modest protein binding of olopatadine (55%), drug interactions through displacement from plasma proteins are also not expected.

13 NONCLINICAL TOXICOLOGY

13.1 Carcinogenesis, Mutagenesis, Impairment of Fertility

Olopatadine administered orally was not carcinogenic in mice and rats at doses of up to 500 mg/kg/day and 200 mg/kg/day, respectively (approximately 420 and 340 times the MRHD for adults and adolescents ≥12 years of age and 500 and 400 times the MRHD for children 6-11 years of age by intranasal administration on a mg/m2 basis, respectively).

There was no evidence of genotoxicity when olopatadine was tested in an in vitro bacteria reverse mutation test (Ames), an in vitro mammalian chromosome aberration assay or an in vivo mouse micronucleus test.

Olopatadine administered orally to male and female rats at dose of 400 mg/kg/day, (approximately 680 times the MRHD for adults on a mg/m2 basis) resulted in a decrease in the fertility index and reduced implantation rate. No effects on fertility were observed at dose of 50 mg/kg/day (approximately 85 times the MRHD for adults on a mg/m2 basis).

13.2 Animal Toxicology

Reproductive Toxicology Studies

Olopatadine was not teratogenic in rabbits and rats at oral doses of up to 400 or 600 mg/kg/day, respectively (approximately 1,400 and 1,000 times the MRHD for adults on a mg/m2 basis, respectively). However, a decrease in the number of live fetuses was observed in rabbits at the oral olopatadine doses of 25 mg/kg (approximately 88 times the MRHD for adults on a mg/m2 basis) and above, and in rats at oral doses of 60 mg/kg (approximately 100 times the MRHD for adults on a mg/m2 basis) and above. In rats, viability and body weights of pups were reduced on day 4 post partum at the oral doses of 60 mg/kg (approximately 100 times the MRHD for adults on a mg/m2 basis) and above, but no effect on viability was observed at the dose of 20 mg/kg (approximately 35 times the MRHD for adults on a mg/m2 basis).

14 CLINICAL STUDIES

14.1 Seasonal Allergic Rhinitis

Adult and Adolescent Patients 12 Years of Age and Older:

The efficacy and safety of PATANASE Nasal Spray were evaluated in three randomized, double blind, parallel group, multicenter, placebo (vehicle nasal spray)-controlled clinical trials of 2 weeks duration in adult and adolescent patients, 12 years of age and older with symptoms of seasonal allergic rhinitis. The three clinical trials were conducted in the United States and included 1,598 patients (556 males, and 1,042 females) 12 years of age and older. In these three trials 587 patients were treated with PATANASE Nasal Spray 0.6%, 418 patients were treated with PATANASE Nasal Spray 0.4%, and 593 patients were treated with vehicle nasal spray. Assessment of efficacy was based on patient recording of 4 individual nasal symptoms (nasal congestion, rhinorrhea, itchy nose, and sneezing) on a 0 to 3 categorical severity scale (0 = absent, 1 = mild, 2 = moderate, 3 = severe) as reflective or instantaneous scores. Reflective scoring required patients to record symptom severity over the previous 12 hours; the instantaneous scoring required patients to record symptom severity at the time of recording. The primary efficacy endpoint was the difference from placebo in the percent change from baseline in the average of morning and evening reflective total nasal symptom score (rTNSS) averaged for the 2-week treatment period. In all 3 trials, patients treated with PATANASE Nasal Spray, two sprays per nostril, twice-daily, exhibited statistically significantly greater decreases in rTNSS compared to vehicle nasal spray. Results for the rTNSS from two representative trials are shown in Table 3.

Table 3: Mean Reflective Total Nasal Symptom Score (rTNSS) in Adult and Adolescent Patients with Seasonal Allergic Rhinitis

 | Treatment | N | Baseline | Change from Baseline | Difference from Placebo
 |  |  |  |  | Estimate | 95% CI | p-value
Study 1 | PATANASE Nasal Spray 0.6% | 183 | 8.71 | -3.63 | -0.96 | (-1.42, -0.51) | <0.0001
 | PATANASE Nasal Spray 0.4% | 188 | 8.90 | -3.38 | -0.71 | (-1.17, -0.26) | 0.0023
 | Vehicle Nasal Spray | 191 | 8.75 | -2.67
Study 2 | PATANASE Nasal Spray 0.6% | 220 | 9.17 | -2.90 | -0.98 | (-1.37, -0.59) | <0.0001
 | PATANASE Nasal Spray 0.4% | 228 | 9.26 | -2.63 | -0.72 | (-1.11, -0.33) | 0.0003
 | Vehicle Nasal Spray | 223 | 9.07 | -1.92

Itchy eyes and watery eyes were evaluated as secondary endpoints but eye redness was not evaluated. In two of the studies, patients treated with PATANASE Nasal Spray had significantly greater decreases in reflective symptom scores for itchy eyes and watery eyes, compared to vehicle nasal spray.

In the 2-week seasonal allergy trials, onset of action was also evaluated by instantaneous TNSS assessments twice-daily after the first dose of study medication. In these trials, onset of action was seen after 1 day of dosing. Onset of action was evaluated in three environmental exposure unit studies with single doses of PATANASE Nasal Spray. In these studies, patients with seasonal allergic rhinitis were exposed to high levels of pollen in the environmental exposure unit and then treated with either PATANASE Nasal Spray or vehicle nasal spray, two sprays in each nostril, after which they self-reported their allergy symptoms hourly as instantaneous scores for the subsequent 12 hours. PATANASE Nasal Spray 0.6% was found to have an onset of action of 30 minutes after dosing in the environmental exposure unit.

Pediatric Patients 6 to 11Years of Age:

There were 3 clinical trials of 2 weeks duration with olopatadine nasal spray in patients 6 to 11 years of age with seasonal allergic rhinitis. Efficacy of Patanase Nasal Spray was evaluated in 2 of the 3 trials. One of the 2 trials that showed efficacy was a randomized, double blind, parallel group, multicenter, placebo (vehicle nasal spray)-controlled clinical trial of 2 weeks duration including 1,188 children ages 6 to < 12 years with seasonal allergic rhinitis. Assessment of efficacy was based on patient/caregiver recording of 4 individual nasal symptoms (nasal congestion, rhinorrhea, itchy nose, and sneezing) on a 0 to 3 categorical severity scale (0 = absent, 1 = mild, 2 = moderate, 3 = severe) as reflective or instantaneous scores. Reflective scoring captured symptom severity over the previous 12 hours; the instantaneous scoring captured symptom severity at the time of recording. The primary efficacy endpoint was the difference from placebo in the percent change from baseline in the average of patient/caregiver-reported morning and evening reflective total nasal symptom score (rTNSS) averaged for the 2-week treatment period. Patients treated with PATANASE Nasal Spray, 1 or 2 sprays per nostril twice daily, had statistically significantly greater decreases in rTNSS compared to vehicle nasal spray. Results for rTNSS are shown in Table 4.

Table 4: Mean Reflective Total Nasal Symptom Score (rTNSS) in Pediatric Patients 6-11 Years of Age with Seasonal Allergic Rhinitis

Treatment | N | Baseline | Change from Baseline | Difference from Placebo
 |  |  |  | Estimate | 95% CI | p-value
PATANASE Nasal Spray 0.6%, 1 spray per nostril twice daily | 294 | 8.99 | -2.24 | -0.55 | (-0.90, -0.19) | 0.0015
Vehicle Nasal Spray, 1 spray per nostril twice daily | 294 | 9.09 | -1.70

Itchy eyes and watery eyes were evaluated as secondary endpoints in the same study but eye redness was not evaluated. Patients treated with PATANASE Nasal Spray had significantly greater decreases in reflective symptom scores for itchy eyes and watery eyes, compared to vehicle nasal spray.

16 HOW SUPPLIED/STORAGE AND HANDLING

16.1 How Supplied

PATANASE Nasal Spray, 665 mcg is supplied in a white plastic bottle with a metered-dose manual spray pump, a white nasal applicator and a blue overcap in a box of 1 (NDC 54868-6049-0). Each trade size bottle contains 30.5 g of clear, colorless liquid and will provide 240 metered sprays. After priming [see Dosage and Administration (2)], each spray delivers a fine mist containing 665 mcg of olopatadine hydrochloride in 100 microliters of formulation through the nozzle.

Before initial use, prime PATANASE Nasal Spray by releasing 5 sprays or until a fine mist appears. After periods of non-use greater than 7 days, re-prime PATANASE Nasal Spray by releasing 2 sprays. The correct amount of medication cannot be assured before the initial priming and after 240 sprays have been used, even though the bottle is not completely empty. The nasal device should be discarded after 240 sprays (enough for 30 days of dosing) have been used.

Net content 30.5 g, 240 sprays: NDC 54868-6049-0 (trade size)

16.2 Storage

Store at 4° to 25° C (39° to 77° F). Rx Only.

17 PATIENT COUNSELING INFORMATION

See FDA-approved Patient Labeling accompanying the product.

17.1 Local Nasal Effects and Other Common Adverse Reactions

Patients should be informed that treatment with PATANASE Nasal Spray may lead to adverse reactions, which include epistaxis and nasal ulcerations. [see Warnings and Precautions (5.1)] Other common adverse reactions reported with use of PATANASE Nasal Spray include bitter taste, headache, and pharyngolaryngeal pain, [see Adverse Reactions (6)].

17.2. Activities Requiring Mental Alertness

Somnolence has been reported in some patients taking PATANASE Nasal Spray. Patients should be cautioned against engaging in hazardous occupations requiring complete mental alertness and motor coordination such as driving or operating machinery after administration of PATANASE Nasal Spray [see Warnings and Precautions (5.2)].

17.3 Concurrent Use of Alcohol and other Central Nervous System Depressants

Concurrent use of PATANASE Nasal Spray with alcohol or other central nervous system depressants should be avoided because additional reductions in alertness and additional impairment of central nervous system performance may occur [see Warnings and Precautions (5.2)].

17.4 Keep Spray Out of Eyes

Patients should be informed to avoid spraying PATANASE Nasal Spray in their eyes.

U.S. Pat. No. 5,116,863

Revised: April 2010

Mfd for:

ALCON LABORATORIES, INC.

Fort Worth, Texas 76134 USA

Mfd by:

ALCON CUSI, S.A.

08320 El Masnou-Barcelona

Spain

© 2009, 2010 Alcon, Inc.

6-15-332

Additional barcode labeling by:
Physicians Total Care, Inc.
Tulsa, Oklahoma 74146

PATIENT INFORMATION

PATANASE® (PAT-uh-nase)

(olopatadine hydrochloride)

Nasal Spray

For Use in the nose (Intranasal) only.

Read the Patient Information that comes with PATANASE Nasal Spray carefully before you start using it and each time you get a refill. There may be new information. This leaflet does not take the place of talking to your health care provider about your medical condition or your treatment.

What is PATANASE Nasal Spray?

PATANASE Nasal Spray is a prescription medicine used to provide relief of seasonal allergy symptoms in adults and children 6 years and older.

PATANASE Nasal Spray contains an antihistamine medicine that may help reduce nasal symptoms of seasonal allergic rhinitis.

What should I tell my health care provider before taking PATANASE Nasal Spray?

Tell your health care provider about all your medical conditions, including if you are:

• allergic to any of the ingredients in PATANASE Nasal Spray. See the end of this leaflet for a complete list of the ingredients in PATANASE Nasal Spray.

• pregnant or planning to become pregnant. It is not known if PATANASE Nasal Spray will harm your unborn baby.

• breast-feeding a baby. It is not known if PATANASE Nasal Spray passes into your breast milk.

Tell your health care provider about all the medicines you take, including prescription and nonprescription medicines, vitamins, and herbal products. PATANASE Nasal Spray and other medicines may affect each other, causing side effects.

Know the medicines you take. Keep a list of your medicines and show it to your doctor and pharmacist when you get a new medicine.

How should I use PATANASE Nasal Spray?

• PATANASE Nasal Spray is for use in the nose only. Do not spray it in your eyes or mouth.

• Use PATANASE Nasal Spray exactly as your health care provider tells you. Do not stop taking PATANASE Nasal Spray without talking to your health care provider.

• This nasal device should be discarded after the labeled number of sprays (240) or after

the expiration date on the medicine label or box.

• Do not use PATANASE Nasal Spray after the expiration date on the medicine label and box.

Follow the Patient Instructions for Use below.

What are the possible side effects of PATANASE Nasal Spray?

Side effects of PATANASE Nasal Spray include:

• bad or bitter taste

• headache

• nosebleeds

• sores in your nose

• hole in the nasal septum

Tell your health care provider if you have any side effect that bothers you or does not go away.

These are not all of the possible side effects of PATANASE Nasal Spray. For more information, ask your health care provider or pharmacist.

Call your doctor for medical advice about side effects. You may report side effects to FDA at 1-800-FDA-1088.

What should I avoid while using PATANASE Nasal Spray?

PATANASE Nasal Spray can make you sleepy.

Avoid the following while using PATANASE Nasal Spray:

• operating machinery, driving a motor vehicle, or doing other dangerous activities

• using alcohol or other medicines that can also make you sleepy, such as sedatives and tranquilizers

General information about PATANASE Nasal Spray

Medicines are sometimes prescribed for conditions that are not mentioned in the patient leaflet. Do not use PATANASE Nasal Spray for a condition for which it was not prescribed. Do not give PATANASE Nasal Spray to other people, even if they have the same symptoms you have. It may harm them.

This patient information leaflet summarizes the most important information about PATANASE Nasal Spray. If you would like more information about PATANASE Nasal Spray talk with your health care provider. You can ask your health care provider or pharmacist for information about PATANASE Nasal Spray that is written for health professionals. For more information go to www.PATANASE.com or call 1-800-757-9195.

What are the ingredients of PATANASE Nasal Spray?

Active ingredient: olopatadine hydrochloride 665 micrograms per 100 microliter spray.

Inactive ingredients: 0.01% benzalkonium chloride, sodium phosphate, dibasic, edentate disodium, sodium chloride, hydrochloric acid, sodium hydroxide and water.

What should I know about seasonal allergic rhinitis?

"Rhinitis" means inflammation of the lining of the nose. Seasonal allergic rhinitis is sometimes called "hay fever". Seasonal allergic rhinitis can be caused by allergies to pollen. If you have allergic rhinitis, your nose becomes stuffy, runny and itchy. You may also sneeze a lot. You may also have red, itchy, watery eyes and itchy throat, or blocked itchy ears.

PHARMACIST Give to Patient

Patient Instructions for Use

Rx Only

For use in the nose (Intranasal) only

Use PATANASE® Nasal Spray exactly how your doctor tells you to. The usual dose of PATANASE Nasal Spray for people ages 12 and older is two sprays in each nostril, two times each day and for children 6 to 11, one spray in each nostril two times a day.

1. Remove the blue plastic overcap (Figure 1).

2. Hold the bottle and press down on the shoulders of the white nasal applicator with your forefinger and middle finger.

Support the bottom (base) of the bottle with your thumb while you do this (Figure 2). Prime the bottle five (5) times or until you see a fine mist come out of the nasal spray applicator. After you start using a bottle of PATANASE Nasal Spray, if you do not use it for more than seven (7) days, you will need to prime the pump again two (2) times before use.

3. Gently blow your nose to clear the nostrils. Close one nostril. With your head tipped down (chin toward chest), place the nasal applicator 1/4 to 1/2 inch into a nostril. Hold the medicine bottle upright with the nasal applicator tip aimed toward the cheek side of the nose, away from the center of the nose (Figure 3).

4. Breathe in gently through your nose. While breathing in press firmly and quickly on the applicator to release the spray (Figure 3).

5. Breathe out through your mouth. Do not tip your head back or blow your nose right after using PATANASE Nasal Spray. This may cause you to get a bitter taste in your mouth.

6. Change between the nostrils (alternate). Spray two sprays in each nostril.

7. Wipe the nasal applicator with a clean tissue and replace the blue plastic overcap. (Figure 4)

8. This nasal device should be discarded after the labeled number of sprays (240) or after the expiration date on the medicine label or box.

9. Do not take extra doses or stop taking PATANASE Nasal Spray without talking with your doctor.

1. If the nasal applicator becomes clogged, do not attempt to clear it using a pointed object. (Figure 5)

2. To clean the nasal applicator, remove the plastic cap and then gently pull upwards to free the nasal applicator. (Figure 6 & 7)

3. With the nasal applicator pointing downwards, wash by running warm tap water into the nasal applicator for about one minute. (Figure 8)

4. Shake the applicator to remove any water and put the applicator back on the bottle.

5. Prime by spraying two (2) times or until you see a fine mist.

6. Repeat the above steps if needed.

• Store PATANASE Nasal Spray between 39° to 77°F (4° to 25°C).

• Do not use your PATANASE Nasal Spray after the expiration date on the label or box.

Keep PATANASE Nasal Spray and all medicines out of the reach of children.

For more information about PATANASE Nasal Spray visit www.PATANASE.com or call 1-800-757-9195.

Mfd. for:

ALCON LABORATORIES, INC.

Fort Worth, Texas 76134 USA

Mfd. by:

ALCON CUSI, S.A.

08320 El Masnou - Barcelona

Spain

© 2008, 2009 Alcon, Inc.

Revised: December 2009

6-15-323

PRINCIPAL DISPLAY PANEL

FOR INTRANASAL USE ONLY

Rx Only

NDC 54868-6049-0

Patanase®

(olopatadine hydrochloride)

Nasal Spray, 665 mcg

240 Metered Sprays

Net Fill Weight 30.5g